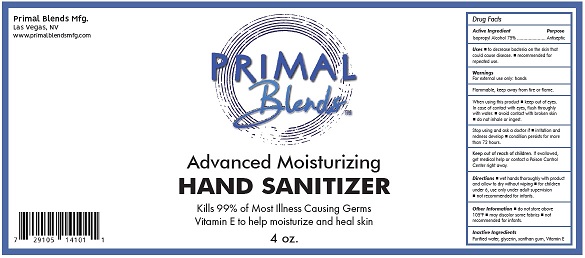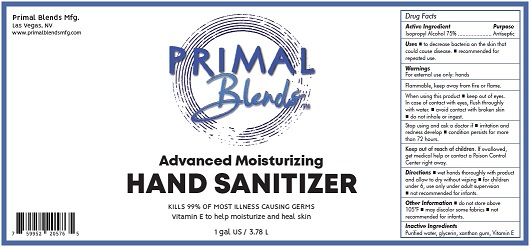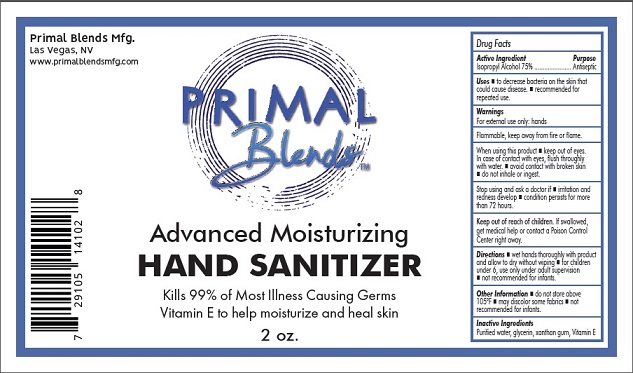 DRUG LABEL: Primal Blends Advanced Moisturizing Hand Sanitizer
NDC: 75494-001 | Form: LIQUID
Manufacturer: Alchemy Nutra LLC
Category: otc | Type: HUMAN OTC DRUG LABEL
Date: 20200416

ACTIVE INGREDIENTS: ISOPROPYL ALCOHOL 75 mL/100 mL
INACTIVE INGREDIENTS: GLYCERIN; .ALPHA.-TOCOPHEROL; WATER

Active Ingredient

Isopropyl Alcohol 75% v/v.

Purpose

Antiseptic

Uses

To decrease bacteria on the skin that could cause disease.

recommended for repeated use

Warnings

For external use only

Flammable, keep away from fire or flame

When using this product keep out of eyes. In case of contact with eyes, flush throughlywith water. Avoid contact with broken skin.

Stop using and ask a doctor if irritation and redness develops, condition persists for more than 72 hours.

Keep out of reach of children

If swallowed, get medical help or contact a Poison Control Center right away.

Directions

Wet hands thoroughly with product and allow to dry without wiping

For children under 6, use only under adult supervision

Not recommended for infants

Other Information: Do not store above 105°F. May discolor some fabrics.

Inactive ingredients

Purified water, glycerin, Vitamin E

Package Label - Principal Display Panel

59 mL Label

118 mL Label

3780 mL Label